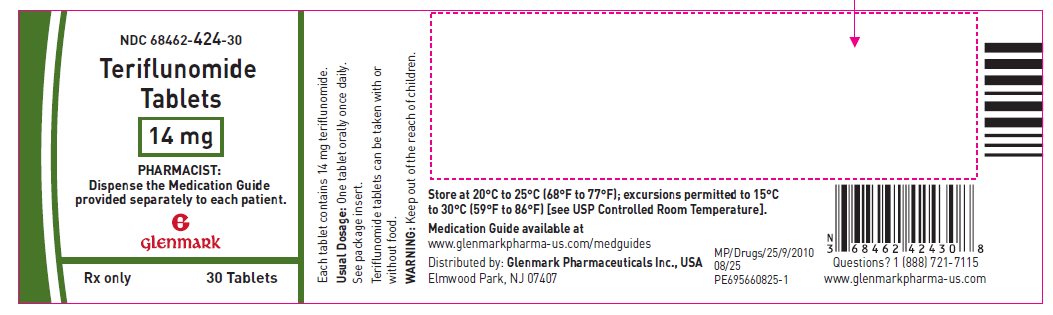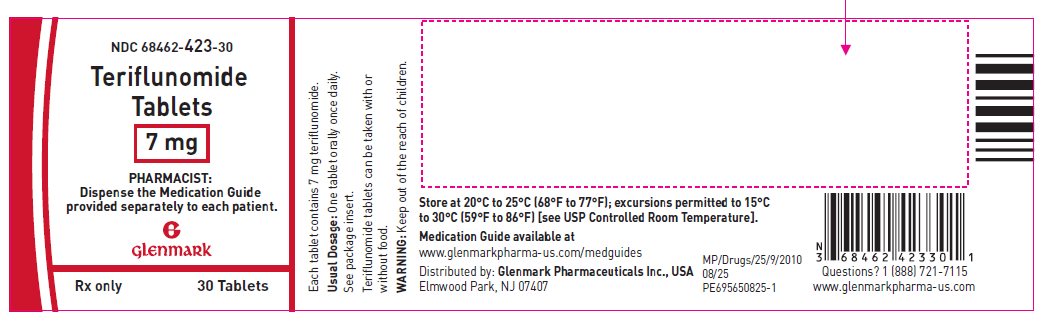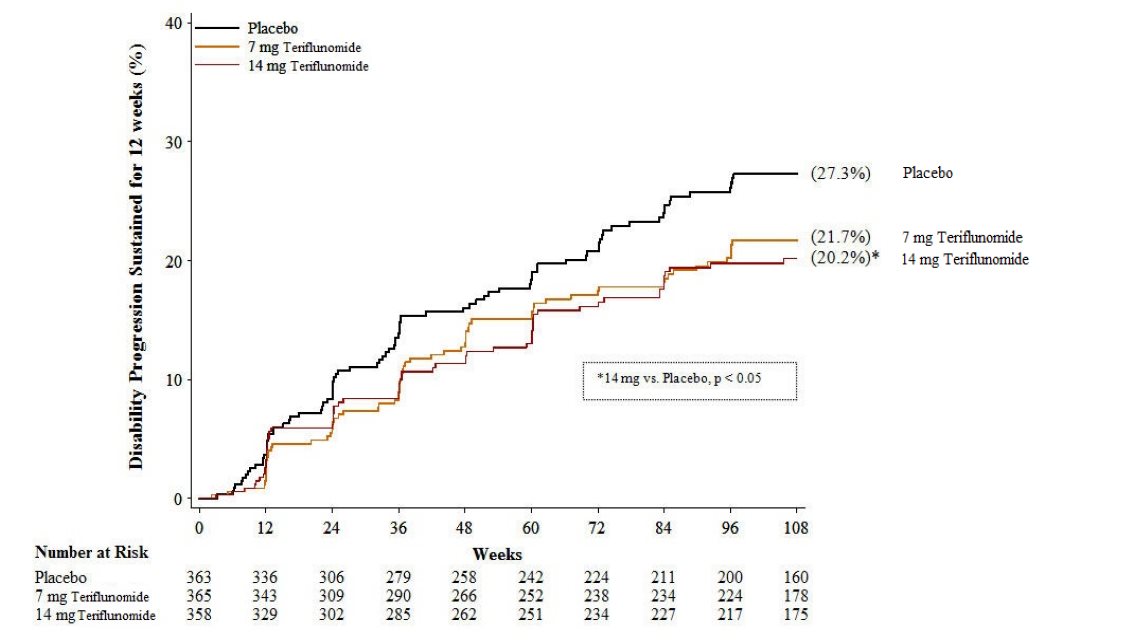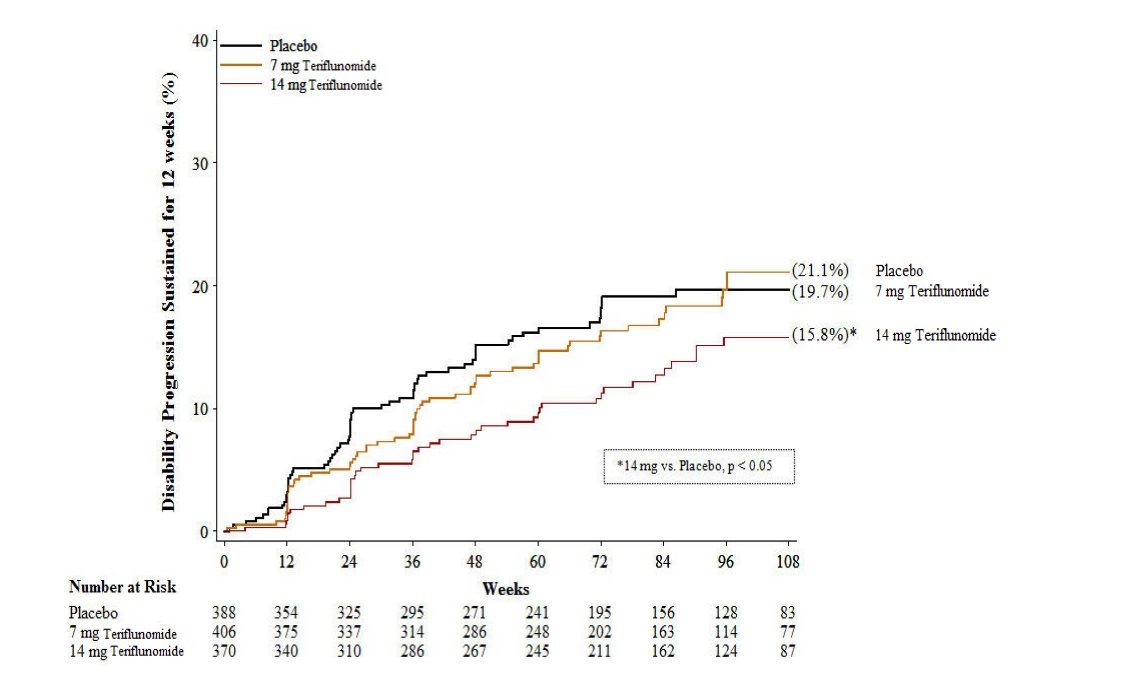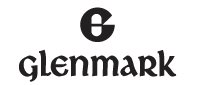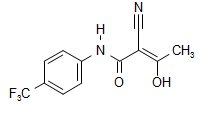 DRUG LABEL: teriflunomide
NDC: 68462-423 | Form: TABLET, FILM COATED
Manufacturer: Glenmark Pharmaceuticals Inc., USA
Category: prescription | Type: HUMAN PRESCRIPTION DRUG LABEL
Date: 20260129

ACTIVE INGREDIENTS: teriflunomide 7 mg/1 1
INACTIVE INGREDIENTS: STARCH, CORN; SILICON DIOXIDE; HYDROXYPROPYL CELLULOSE, UNSPECIFIED; LACTOSE MONOHYDRATE; MAGNESIUM STEARATE; MICROCRYSTALLINE CELLULOSE; SODIUM STARCH GLYCOLATE TYPE A POTATO; HYPROMELLOSE, UNSPECIFIED; POLYETHYLENE GLYCOL 400; TALC; TITANIUM DIOXIDE; FERRIC OXIDE YELLOW

HIGHLIGHTS OF PRESCRIBING INFORMATION

These highlights do not include all the information needed to use TERIFLUNOMIDE TABLETS safely and effectively. See full prescribing information for TERIFLUNOMIDE TABLETS.
TERIFLUNOMIDE tablets, for oral use
Initial U.S. Approval: 2012

WARNING: HEPATOTOXICITY and EMBRYOFETAL TOXICITY

See full prescribing information for complete boxed warning

- Hepatotoxicity

Clinically significant and potentially life-threatening liver injury, including acute liver failure requiring transplant, has been reported in patients treated with teriflunomide in the postmarketing setting (5.1). Concomitant use of teriflunomide with other hepatotoxic drugs may increase the risk of severe liver injury. Obtain transaminase and bilirubin levels within 6 months before initiation of teriflunomide and monitor ALT levels at least monthly for six months (5.1). If drug induced liver injury is suspected, discontinue teriflunomide and start accelerated elimination procedure (5.3).

- Embryofetal Toxicity

Teratogenicity and embryolethality occurred in animals administered teriflunomide (5.2, 8.1). Exclude pregnancy prior to initiating teriflunomide therapy (4, 5.2, 8.1, 8.3). Advise use of effective contraception in females of reproductive potential during treatment and during an accelerated drug elimination procedure (4, 5.2, 5.3, 8.1, 8.3). Stop teriflunomide and use an accelerated drug elimination procedure if the patient becomes pregnant (5.2, 5.3, 8.1).

1 INDICATIONS AND USAGE

Teriflunomide is a pyrimidine synthesis inhibitor indicated for the treatment of relapsing forms of multiple sclerosis (MS), to include clinically isolated syndrome, relapsing-remitting disease, and active secondary progressive disease, in adults. (1)

2 DOSAGE AND ADMINISTRATION

7 mg or 14 mg orally once daily, with or without food. (2)

3 DOSAGE FORMS AND STRENGTHS

7 mg and 14 mg film-coated tablets (3)

4 CONTRAINDICATIONS

- Severe hepatic impairment (4, 5.1)
- Pregnancy (4, 5.2, 8.1)
- Hypersensitivity (4, 5.5)
- Current leflunomide treatment (4)

5 WARNINGS AND PRECAUTIONS

- Elimination of teriflunomide can be accelerated by administration of cholestyramine or activated charcoal for 11 days. (5.3)
- Teriflunomide may decrease WBC. A recent CBC should be available before starting teriflunomide. Monitor for signs and symptoms of infection. Consider suspending treatment with teriflunomide in case of serious infection. Do not start teriflunomide in patients with active infections. (5.4)
- Stop teriflunomide if patient has anaphylaxis, angioedema, Stevens-Johnson syndrome, toxic epidermal necrolysis, drug reaction with eosinophilia and systemic symptoms; initiate rapid elimination. (5.3, 5.5, 5.6, 5.7)
- If patient develops symptoms consistent with peripheral neuropathy, evaluate patient and consider discontinuing teriflunomide. (5.8)
- Teriflunomide may increase blood pressure. Measure blood pressure at treatment initiation and monitor blood pressure during treatment. (5.9)

6 ADVERSE REACTIONS

Most common adverse reactions (≥10% and ≥2% greater than placebo): headache, diarrhea, nausea, alopecia, increase in ALT. (6)

To report SUSPECTED ADVERSE REACTIONS, contact Glenmark Pharmaceuticals Inc., USA at 1 (888) 721-7115 or FDA at 1-800-FDA-1088 or www.fda.gov/medwatch.

7 DRUG INTERACTIONS

- Drugs metabolized by CYP2C8 and OAT3 transporters: Monitor patients because teriflunomide may increase exposure of these drugs. (7)
- Teriflunomide may increase exposure of ethinylestradiol and levonorgestrel. Choose an appropriate oral contraceptive. (7)
- Drugs metabolized by CYP1A2: Monitor patients because teriflunomide may decrease exposure of these drugs. (7)
- Warfarin: Monitor INR as teriflunomide may decrease INR. (7)
- Drugs metabolized by BCRP and OATP1B1/B3 transporters: Monitor patients because teriflunomide may increase exposure of these drugs. (7)
- Rosuvastatin: The dose of rosuvastatin should not exceed 10 mg once daily in patients taking teriflunomide. (7)

FULL PRESCRIBING INFORMATION

WARNING: HEPATOTOXICITY and EMBRYOFETAL TOXICITY

- Hepatotoxicity

Clinically significant and potentially life-threatening liver injury, including acute liver failure requiring transplant, has been reported in patients treated with teriflunomide in the postmarketing setting [see Warnings and Precautions (5.1)]. Concomitant use of teriflunomide with other hepatotoxic drugs may increase the risk of severe liver injury.

Obtain transaminase and bilirubin levels within 6 months before initiation of teriflunomide therapy. Monitor ALT levels at least monthly for six months after starting teriflunomide [see Warnings and Precautions (5.1)]. If drug induced liver injury is suspected, discontinue teriflunomide and start an accelerated elimination procedure with cholestyramine or charcoal [see Warnings and Precautions (5.3)]. Teriflunomide is contraindicated in patients with severe hepatic impairment [see Contraindications (4)]. Patients with pre-existing liver disease may be at increased risk of developing elevated serum transaminases when taking teriflunomide.

- Embryofetal Toxicity

Teriflunomide is contraindicated for use in pregnant women and in females of reproductive potential who are not using effective contraception because of the potential for fetal harm. Teratogenicity and embryolethality occurred in animals at plasma teriflunomide exposures lower than that in humans. Exclude pregnancy before the start of treatment with teriflunomide in females of reproductive potential. Advise females of reproductive potential to use effective contraception during teriflunomide treatment and during an accelerated drug elimination procedure after teriflunomide treatment. Stop teriflunomide and use an accelerated drug elimination procedure if the patient becomes pregnant [see Contraindications (4), Warnings and Precautions (5.2, 5.3), Use in Specific Populations (8.1, 8.3), and Clinical Pharmacology (12.3)].

1 INDICATIONS AND USAGE

Teriflunomide tablets are indicated for the treatment of relapsing forms of multiple sclerosis (MS), to include clinically isolated syndrome, relapsing-remitting disease, and active secondary progressive disease, in adults.

2 DOSAGE AND ADMINISTRATION

The recommended dose of teriflunomide tablet is 7 mg or 14 mg orally once daily. Teriflunomide tablets can be taken with or without food.

Monitoring to Assess Safety

- Obtain transaminase and bilirubin levels within 6 months before initiation of teriflunomide tablets therapy. Monitor ALT levels at least monthly for six months after starting teriflunomide tablets [see Warnings and Precautions (5.1)].
- Obtain a complete blood cell count (CBC) within 6 months before the initiation of treatment with teriflunomide tablets. Further monitoring should be based on signs and symptoms of infection [see Warnings and Precautions (5.4)].
- Prior to initiating teriflunomide tablets, screen patients for latent tuberculosis infection with a tuberculin skin test or blood test for mycobacterium tuberculosis infection [see Warnings and Precautions (5.4)].
- Exclude pregnancy prior to initiation of treatment with teriflunomide tablets in females of reproductive potential [see Warnings and Precautions (5.2)].
- Check blood pressure before start of teriflunomide tablets treatment and periodically thereafter [see Warnings and Precautions (5.9)].

3 DOSAGE FORMS AND STRENGTHS

Teriflunomide is available as 7 mg and 14 mg tablets.

The 14 mg tablet is a white to off-white, biconvex, round film-coated tablet debossed with ‘G’ on one side and ‘42’ on the other side. Each tablet contains 14 mg of teriflunomide.

The 7 mg tablet is a light yellow to yellow, biconvex, round film-coated tablet debossed with ‘G’ on one side and ‘43’ on the other side. Each tablet contains 7 mg of teriflunomide.

4 CONTRAINDICATIONS

Teriflunomide tablets are contraindicated in/with:

- Patients with severe hepatic impairment [see Warnings and Precautions (5.1)].
- Pregnant women and females of reproductive potential not using effective contraception. Teriflunomide may cause fetal harm [see Warnings and Precautions (5.2, 5.3) and Use in Specific Populations (8.1)].
- Patients with a history of a hypersensitivity reaction to teriflunomide, leflunomide, or to any of the inactive ingredients in teriflunomide tablets. Reactions have included anaphylaxis, angioedema, and serious skin reactions [see Warnings and Precautions (5.5)].
- Coadministration with leflunomide [see Clinical Pharmacology (12.3)].

5 WARNINGS AND PRECAUTIONS

5.1 Hepatotoxicity

Clinically significant and potentially life-threatening liver injury, including acute liver failure requiring transplant, has been reported in patients treated with teriflunomide in the postmarketing setting. Patients with pre-existing liver disease and patients taking other hepatotoxic drugs may be at increased risk for developing liver injury when taking teriflunomide. Clinically significant liver injury can occur at any time during treatment with teriflunomide.

Patients with pre-existing acute or chronic liver disease, or those with serum alanine aminotransferase (ALT) greater than two times the upper limit of normal (ULN) before initiating treatment, should not normally be treated with teriflunomide. Teriflunomide is contraindicated in patients with severe hepatic impairment [see Contraindications (4)].

In placebo-controlled trials in adult patients, ALT greater than three times the ULN occurred in 61/1045 (5.8%) and 62/1002 (6.2%) of patients receiving teriflunomide 7 mg and 14 mg, respectively, and 38/997 (3.8%) of patients receiving placebo, during the treatment period. These elevations occurred mostly within the first year of treatment. Half of the cases returned to normal without drug discontinuation. In clinical trials, if ALT elevation was greater than three times the ULN on two consecutive tests, teriflunomide was discontinued and patients underwent an accelerated elimination procedure [see Warnings and Precautions (5.3)]. Of the patients who underwent discontinuation and accelerated elimination in controlled trials, half returned to normal or near normal values within 2 months.

One patient in the controlled trials in adult patients developed ALT 32 times the ULN and jaundice 5 months after initiation of teriflunomide 14 mg treatment. The patient was hospitalized for 5 weeks and recovered after plasmapheresis and cholestyramine accelerated elimination procedure. Teriflunomide-induced liver injury in this patient could not be ruled out.

Obtain serum transaminase and bilirubin levels within 6 months before initiation of teriflunomide therapy. Monitor ALT levels at least monthly for six months after starting teriflunomide. Consider additional monitoring when teriflunomide is given with other potentially hepatotoxic drugs.

Consider discontinuing teriflunomide if serum transaminase increase (greater than three times the ULN) is confirmed. Monitor serum transaminase and bilirubin on teriflunomide therapy, particularly in patients who develop symptoms suggestive of hepatic dysfunction, such as unexplained nausea, vomiting, abdominal pain, fatigue, anorexia, or jaundice and/or dark urine. If liver injury is suspected to be teriflunomide-induced, discontinue teriflunomide and start an accelerated elimination procedure [see Warnings and Precautions (5.3)] and monitor liver tests weekly until normalized. If teriflunomide-induced liver injury is unlikely because some other probable cause has been found, resumption of teriflunomide therapy may be considered.

5.2 Embryofetal Toxicity

Teriflunomide may cause fetal harm when administered to a pregnant woman. Teratogenicity and embryofetal lethality occurred in animal reproduction studies in multiple animal species at plasma teriflunomide exposures similar to or lower than that in humans at the maximum recommended human dose (MRHD) of 14 mg/day [see Use in Specific Populations (8.1)].

Teriflunomide is contraindicated for use in pregnant women and in females of reproductive potential not using effective contraception [see Contraindications (4)]. Exclude pregnancy before starting treatment with teriflunomide in females of reproductive potential [see Dosage and Administration (2)]. Advise females of reproductive potential to use effective contraception during teriflunomide treatment and during an accelerated drug elimination procedure after teriflunomide treatment [see Use in Specific Populations (8.3)]. If a woman becomes pregnant while taking teriflunomide, stop treatment with teriflunomide, apprise the patient of the potential risk to a fetus, and perform an accelerated drug elimination procedure to achieve a plasma teriflunomide concentration of less than 0.02 mg/L [see Warnings and Precautions (5.3)].

Upon discontinuing teriflunomide, it is recommended that all females of reproductive potential undergo an accelerated drug elimination procedure. Women receiving teriflunomide treatment who wish to become pregnant must discontinue teriflunomide and undergo an accelerated drug elimination procedure, which includes verification that plasma concentrations of teriflunomide are less than 0.02 mg/L (0.02 mcg/mL). Men wishing to father a child should also discontinue use of teriflunomide and either undergo an accelerated elimination procedure or wait until verification that the plasma teriflunomide concentration is less than 0.02 mg/L (0.02 mcg/mL) [see Use in Specific Populations (8.3)]. Based on animal data, human plasma concentrations of teriflunomide of less than 0.02 mg/L (0.02 mcg/mL) are expected to have minimal embryofetal risk [see Contraindications (4), Warnings and Precautions (5.3), and Use in Specific Populations (8.1)].

5.3 Procedure for Accelerated Elimination of Teriflunomide

Teriflunomide is eliminated slowly from the plasma [see Clinical Pharmacology (12.3)]. Without an accelerated elimination procedure, it takes on average 8 months to reach plasma concentrations less than 0.02 mg/L, although because of individual variations in drug clearance it may take as long as 2 years. An accelerated elimination procedure could be used at any time after discontinuation of teriflunomide. Elimination can be accelerated by either of the following procedures:

- Administration of cholestyramine 8 g every 8 hours for 11 days. If cholestyramine 8 g three times a day is not well tolerated, cholestyramine 4 g three times a day can be used.
- Administration of 50 g oral activated charcoal powder every 12 hours for 11 days.

If either elimination procedure is poorly tolerated, treatment days do not need to be consecutive unless there is a need to lower teriflunomide plasma concentration rapidly.

At the end of 11 days, both regimens successfully accelerated teriflunomide elimination, leading to more than 98% decrease in teriflunomide plasma concentrations.

Use of the accelerated elimination procedure may potentially result in return of disease activity if the patient had been responding to teriflunomide treatment.

5.4 Bone Marrow Effects/Immunosuppression Potential/Infections

Bone Marrow Effects

A mean decrease compared to baseline in white blood cell (WBC) count of approximately 15% (mainly neutrophils and lymphocytes) and in platelet count of approximately 10% was observed in placebo-controlled trials in adult patients with 7 mg and 14 mg of teriflunomide. The decrease in mean WBC count occurred during the first 6 weeks and WBC count remained low during treatment. In placebo-controlled studies in adult patients, neutrophil count <1.5 × 109/L was observed in 12% and 16% of patients receiving teriflunomide 7 mg and 14 mg, respectively, compared with 7% of patients receiving placebo; lymphocyte count <0.8 × 109/L was observed in 10% and 12% of patients receiving teriflunomide 7 mg and 14 mg, respectively, compared with 6% of patients receiving placebo. No cases of serious pancytopenia were reported in premarketing clinical trials of teriflunomide but rare cases of pancytopenia and agranulocytosis have been reported in the postmarketing setting with leflunomide. A similar risk would be expected for teriflunomide [see Clinical Pharmacology (12.3)]. Cases of thrombocytopenia with teriflunomide, including rare cases with platelet counts less than 50,000/mm3, have been reported in the postmarketing setting. Obtain a complete blood cell count (CBC) within 6 months before the initiation of treatment with teriflunomide. Further monitoring should be based on signs and symptoms suggestive of bone marrow suppression.

Risk of Infection / Tuberculosis Screening

Patients with active acute or chronic infections should not start treatment until the infection(s) is resolved. If a patient develops a serious infection consider suspending treatment with teriflunomide and using an accelerated elimination procedure. Reassess the benefits and risks prior to resumption of therapy. Instruct patients receiving teriflunomide to report symptoms of infections to a physician.

Teriflunomide is not recommended for patients with severe immunodeficiency, bone marrow disease, or severe, uncontrolled infections. Medications like teriflunomide that have immunosuppression potential may cause patients to be more susceptible to infections, including opportunistic infections.

In placebo-controlled studies of teriflunomide in adult patients, no overall increase in the risk of serious infections was observed with teriflunomide 7 mg (2.2%) or 14 mg (2.7%) compared to placebo (2.2%).

However, one fatal case of klebsiella pneumonia sepsis occurred in a patient taking teriflunomide 14 mg for 1.7 years. Fatal infections have been reported in the postmarketing setting in patients receiving leflunomide, especially Pneumocystis jirovecii pneumonia and aspergillosis. Most of the reports were confounded by concomitant immunosuppressant therapy and/or comorbid illness which, in addition to rheumatoid disease, may predispose patients to infection. In clinical studies with teriflunomide, cytomegalovirus hepatitis reactivation has been observed.

In clinical studies with teriflunomide in adult patients, cases of tuberculosis have been observed. Prior to initiating teriflunomide, screen patients for latent tuberculosis infection with a tuberculin skin test or with a blood test for mycobacterium tuberculosis infection. Teriflunomide has not been studied in patients with a positive tuberculosis screen, and the safety of teriflunomide in individuals with latent tuberculosis infection is unknown. For patients testing positive in tuberculosis screening, treat by standard medical practice prior to therapy with teriflunomide.

Vaccination

No clinical data are available on the efficacy and safety of live vaccinations in patients taking teriflunomide. Vaccination with live vaccines is not recommended. The long half-life of teriflunomide should be considered when contemplating administration of a live vaccine after stopping teriflunomide.

Malignancy

The risk of malignancy, particularly lymphoproliferative disorders, is increased with the use of some immunosuppressive medications. There is a potential for immunosuppression with teriflunomide. No apparent increase in the incidence of malignancies and lymphoproliferative disorders was reported in the teriflunomide clinical trials, but larger and longer-term studies would be needed to determine whether there is an increased risk of malignancy or lymphoproliferative disorders with teriflunomide.

5.5 Hypersensitivity Reactions

Teriflunomide can cause anaphylaxis and severe allergic reactions [see Contraindications (4)]. Signs and symptoms have included dyspnea, urticaria, and angioedema including lips, eyes, throat, and tongue.

Inform patients of the signs and symptoms of anaphylaxis and angioedema.

5.6 Serious Skin Reactions

Cases of serious skin reactions, sometimes fatal, including Stevens-Johnson syndrome (SJS), toxic epidermal necrolysis (TEN), and drug reaction with eosinophilia and systemic symptoms (DRESS) [see Warnings and Precautions (5.7)], have been reported with teriflunomide. Fatal outcomes were reported in one case of TEN and one case of DRESS.

Inform patients of the signs and symptoms that may signal a serious skin reaction. Instruct patients to discontinue teriflunomide and seek immediate medical care should these signs and symptoms occur. Unless the reaction is clearly not drug related, discontinue teriflunomide and begin an accelerated elimination procedure immediately [see Warnings and Precautions (5.3)]. In such cases, patients should not be re-exposed to teriflunomide [see Contraindications (4)].

5.7 Drug Reaction with Eosinophilia and Systemic Symptoms

Drug reaction with eosinophilia and systemic symptoms (DRESS), also known as multiorgan hypersensitivity, has occurred with teriflunomide. One fatal case of DRESS that occurred in close temporal association (34 days) with the initiation of teriflunomide treatment has been reported in the postmarketing setting. DRESS typically, although not exclusively, presents with fever, rash, lymphadenopathy and/or facial swelling, in association with other organ system involvement, such as hepatitis, nephritis, hematologic abnormalities, myocarditis, or myositis, sometimes resembling an acute viral infection. Eosinophilia is often present. This disorder is variable in its expression, and other organ systems not noted here may be involved. It is important to note that early manifestations of hypersensitivity (e.g., fever, lymphadenopathy) may be present even though rash is not evident. If such signs or symptoms are present, the patient should be evaluated immediately.

Discontinue teriflunomide, unless an alternative etiology for the signs or symptoms is established, and begin an accelerated elimination procedure immediately [see Warnings and Precautions (5.3)]. In such cases, patients should not be re-exposed to teriflunomide [see Contraindications (4)].

5.8 Peripheral Neuropathy

In placebo-controlled studies in adult patients, peripheral neuropathy, including both polyneuropathy and mononeuropathy (e.g., carpal tunnel syndrome), occurred more frequently in patients taking teriflunomide than in patients taking placebo. The incidence of peripheral neuropathy confirmed by nerve conduction studies was 1.4% (13 patients) and 1.9% (17 patients) of patients receiving 7 mg and 14 mg of teriflunomide, respectively, compared with 0.4% receiving placebo (4 patients). Treatment was discontinued in 0.7% (8 patients) with confirmed peripheral neuropathy (3 patients receiving teriflunomide 7 mg and 5 patients receiving teriflunomide 14 mg). Five of them recovered following treatment discontinuation. Not all cases of peripheral neuropathy resolved with continued treatment. Peripheral neuropathy also occurred in patients receiving leflunomide.

Age older than 60 years, concomitant neurotoxic medications, and diabetes may increase the risk for peripheral neuropathy. If a patient taking teriflunomide develops symptoms consistent with peripheral neuropathy, such as bilateral numbness or tingling of hands or feet, consider discontinuing teriflunomide therapy and performing an accelerated elimination procedure [see Warnings and Precautions (5.3)].

5.9 Increased Blood Pressure

In placebo-controlled studies in adult patients, the mean change from baseline to the end of study in systolic blood pressure was +2.3 mmHg and +2.7 mmHg for teriflunomide 7 mg and 14 mg, respectively, and -0.6 mmHg for placebo. The change from baseline in diastolic blood pressure was +1.4 mmHg and +1.9 mmHg for teriflunomide 7 mg and 14 mg, respectively, and -0.3 mmHg for placebo. Hypertension was an adverse reaction in 3.1% and 4.3% of patients treated with 7 mg or 14 mg of teriflunomide compared with 1.8% for placebo. Check blood pressure before start of teriflunomide treatment and periodically thereafter. Elevated blood pressure should be appropriately managed during treatment with teriflunomide.

5.10 Respiratory Effects

Interstitial lung disease, including acute interstitial pneumonitis, has been reported with teriflunomide in the postmarketing setting.

Interstitial lung disease and worsening of pre-existing interstitial lung disease have been reported during treatment with leflunomide. Interstitial lung disease may be fatal and may occur acutely at any time during therapy with a variable clinical presentation. New onset or worsening pulmonary symptoms, such as cough and dyspnea, with or without associated fever, may be a reason for discontinuation of therapy and for further investigation as appropriate. If discontinuation of the drug is necessary, consider initiation of an accelerated elimination procedure [see Warnings and Precautions (5.3)].

5.11 Pancreatitis in Pediatric Patients

Teriflunomide is not approved for use in pediatric patients. In the pediatric clinical trial, cases of pancreatitis were observed in 1.8% (2/109) of patients receiving teriflunomide; one of these cases was serious [see Use in Specific Populations (8.4)]. If pancreatitis is suspected, discontinue teriflunomide and start an accelerated elimination procedure [see Warnings and Precautions (5.3)].

5.12 Concomitant Use with Immunosuppressive or Immunomodulating Therapies

Coadministration with antineoplastic or immunosuppressive therapies used for treatment of multiple sclerosis has not been evaluated. Safety studies in which teriflunomide was concomitantly administered with other immune modulating therapies for up to one year (interferon beta, glatiramer acetate) did not reveal any specific safety concerns. The long term safety of these combinations in the treatment of multiple sclerosis has not been established.

In any situation in which the decision is made to switch from teriflunomide to another agent with a known potential for hematologic suppression, it would be prudent to monitor for hematologic toxicity, because there will be overlap of systemic exposure to both compounds. Use of an accelerated elimination procedure may decrease this risk, but may also potentially result in return of disease activity if the patient had been responding to teriflunomide treatment [see Warnings and Precautions (5.3)].

6 ADVERSE REACTIONS

The following serious adverse reactions are described elsewhere in the prescribing information:

- Hepatotoxicity [see Contraindications (4) and Warnings and Precautions (5.1)]
- Bone Marrow Effects/Immunosuppression Potential/Infections [see Warnings and Precautions (5.4)]
- Hypersensitivity Reactions [see Contraindications (4) and Warnings and Precautions (5.5)]
- Serious Skin Reactions [see Warnings and Precautions (5.6)]
- Drug Reaction with Eosinophilia and Systemic Symptoms [see Warnings and Precautions (5.7)]
- Peripheral Neuropathy [see Warnings and Precautions (5.8)]
- Increased Blood Pressure [see Warnings and Precautions (5.9)]
- Respiratory Effects [see Warnings and Precautions (5.10)]
- Pancreatitis in Pediatric Patients [see Warnings and Precautions (5.11)]

6.1 Clinical Trials Experience

Because clinical trials are conducted under widely varying conditions, adverse reaction rates observed in the clinical trials of a drug cannot be directly compared to rates in the clinical trials of another drug and may not reflect the rates observed in clinical practice.

A total of 2047 patients receiving teriflunomide (7 mg or 14 mg once daily) constituted the safety population in the pooled analysis of placebo-controlled studies in patients with relapsing forms of multiple sclerosis; of these, 71% were female. The average age was 37 years.

Table 1 lists adverse reactions in placebo-controlled trials with rates that were at least 2% for teriflunomide patients and also at least 2% above the rate in placebo patients. The most common were headache, an increase in ALT, diarrhea, alopecia, and nausea. The adverse reaction most commonly associated with discontinuation was an increase in ALT (3.3%, 2.6%, and 2.3% of all patients in the teriflunomide 7 mg, teriflunomide 14 mg, and placebo treatment arms, respectively).

Table 1: Adverse Reactions in Pooled Placebo-Controlled Studies in Patients with Relapsing Forms of Multiple Sclerosis
Adverse Reaction | Teriflunomide 7 mg (N=1045) | Teriflunomide 14 mg (N=1002) | Placebo (N=997)
Headache | 18% | 16% | 15%
Increase in Alanine aminotransferase | 13% | 15% | 9%
Diarrhea | 13% | 14% | 8%
Alopecia | 10% | 13% | 5%
Nausea | 8% | 11% | 7%
Paresthesia | 8% | 9% | 7%
Arthralgia | 8% | 6% | 5%
Neutropenia | 4% | 6% | 2%
Hypertension | 3% | 4% | 2%

Cardiovascular Deaths

Four cardiovascular deaths, including three sudden deaths, and one myocardial infarction in a patient with a history of hyperlipidemia and hypertension were reported among approximately 2600 patients exposed to teriflunomide in the premarketing database. These cardiovascular deaths occurred during uncontrolled extension studies, one to nine years after initiation of treatment. A relationship between teriflunomide and cardiovascular death has not been established.

Acute Renal Failure

In placebo-controlled studies, creatinine values increased more than 100% over baseline in 8/1045 (0.8%) patients in the 7 mg teriflunomide group and 6/1002 (0.6%) patients in the 14 mg teriflunomide group versus 4/997 (0.4%) patients in the placebo group. These elevations were transient. Some elevations were accompanied by hyperkalemia. Teriflunomide may cause acute uric acid nephropathy with transient acute renal failure because teriflunomide increases renal uric acid clearance.

Hypophosphatemia

In clinical trials, 18% of teriflunomide-treated patients had hypophosphatemia with serum phosphorus levels of at least 0.6 mmol/L, compared to 7% of placebo-treated patients; 4% of teriflunomide-treated patients had hypophosphatemia with serum phosphorus levels at least 0.3 mmol/L but less than 0.6 mmol/L, compared to 0.8% of placebo-treated patients. No patient in any treatment group had a serum phosphorus below 0.3 mmol/L.

6.2 Postmarketing Experience

The following adverse reactions have been identified during postapproval use of teriflunomide. Because these reactions are reported voluntarily from a population of uncertain size, it is not always possible to reliably estimate their frequency or establish a causal relationship to drug exposure.

- Blood and Lymphatic System Disorders: Thrombocytopenia [see Warnings and Precautions (5.4)]
- Gastrointestinal Disorders: Pancreatitis, colitis
- Hepatobiliary Disorders: Drug-induced liver injury (DILI) [see Warnings and Precautions (5.1)]
- Immune System Disorders: Hypersensitivity reactions, some of which were severe, such as anaphylaxis and angioedema [see Warnings and Precautions (5.5)]
- Respiratory, Thoracic, and Mediastinal Disorders: Interstitial lung disease [see Warnings and Precautions (5.10)]
- Skin and Subcutaneous Tissue Disorders: Severe skin reactions, including toxic epidermal necrolysis and Stevens-Johnson syndrome [see Warnings and Precautions (5.6)]; drug reaction with eosinophilia and systemic symptoms (DRESS) [see Warnings and Precautions (5.7)]; psoriasis or worsening of psoriasis (including pustular psoriasis and nail psoriasis); nail disorders

7 DRUG INTERACTIONS

Effect of Teriflunomide on CYP2C8 Substrates

Teriflunomide is an inhibitor of CYP2C8 in vivo. In patients taking teriflunomide, exposure of drugs metabolized by CYP2C8 (e.g., paclitaxel, pioglitazone, repaglinide, rosiglitazone) may be increased. Monitor these patients and adjust the dose of the concomitant drug(s) metabolized by CYP2C8 as required [see Clinical Pharmacology (12.3)].

Effect of Teriflunomide on Warfarin

Coadministration of teriflunomide with warfarin requires close monitoring of the international normalized ratio (INR) because teriflunomide may decrease peak INR by approximately 25%.

Effect of Teriflunomide on Oral Contraceptives

Teriflunomide may increase the systemic exposures of ethinylestradiol and levonorgestrel. Consideration should be given to the type or dose of contraceptives used in combination with teriflunomide [see Clinical Pharmacology (12.3)].

Effect of Teriflunomide on CYP1A2 Substrates

Teriflunomide may be a weak inducer of CYP1A2 in vivo. In patients taking teriflunomide, exposure of drugs metabolized by CYP1A2 (e.g., alosetron, duloxetine, theophylline, tizanidine) may be reduced. Monitor these patients and adjust the dose of the concomitant drug(s) metabolized by CYP1A2 as required [see Clinical Pharmacology (12.3)].

Effect of Teriflunomide on Organic Anion Transporter 3 (OAT3) Substrates

Teriflunomide inhibits the activity of OAT3 in vivo. In patients taking teriflunomide, exposure of drugs which are OAT3 substrates (e.g., cefaclor, cimetidine, ciprofloxacin, penicillin G, ketoprofen, furosemide, methotrexate, zidovudine) may be increased. Monitor these patients and adjust the dose of the concomitant drug(s) which are OAT3 substrates as required [see Clinical Pharmacology (12.3)].

Effect of Teriflunomide on BCRP and Organic Anion Transporting Polypeptide B1 and B3 (OATP1B1/1B3) Substrates

Teriflunomide inhibits the activity of BCRP and OATP1B1/1B3 in vivo. For a patient taking teriflunomide, the dose of rosuvastatin should not exceed 10 mg once daily. For other substrates of BCRP (e.g., mitoxantrone) and drugs in the OATP family (e.g., methotrexate, rifampin), especially HMG-Co reductase inhibitors (e.g., atorvastatin, nateglinide, pravastatin, repaglinide, and simvastatin), consider reducing the dose of these drugs and monitor patients closely for signs and symptoms of increased exposures to the drugs while patients are taking teriflunomide [see Clinical Pharmacology (12.3)].

8 USE IN SPECIFIC POPULATIONS

8.1 Pregnancy

Risk Summary

Teriflunomide is contraindicated for use in pregnant women and females of reproductive potential not using effective contraception because of the potential for fetal harm based on animal data [see Contraindications (4) and Warnings and Precautions (5.2)].

In animal reproduction studies in rat and rabbit, oral administration of teriflunomide during organogenesis caused teratogenicity and embryolethality at plasma exposures (AUC) lower than that at the maximum recommended human dose (MRHD) of 14 mg/day [see Data]. Available human data from pregnancy registries, clinical trials, pharmacovigilance cases, and published literature are too limited to draw any conclusions, but they do not clearly indicate increased birth defects or miscarriage associated with inadvertent teriflunomide exposure in the early first trimester when followed by an accelerated elimination procedure [see Clinical Considerations and Data]. There are no human data pertaining to exposures later in the first trimester or beyond.

In the US general population, the estimated background risk of major birth defects and miscarriage in clinically recognized pregnancies is 2% to 4% and 15% to 20%, respectively. The background risk of major birth defects and miscarriage in the indicated population is unknown.

Clinical Considerations

Fetal/Neonatal adverse reactions

Lowering the plasma concentration of teriflunomide by instituting an accelerated drug elimination procedure as soon as pregnancy is detected may decrease the risk to the fetus from teriflunomide. The accelerated drug elimination procedure includes verification that the plasma teriflunomide concentration is less than 0.02 mg/L [see Warnings and Precautions (5.3) and Clinical Pharmacology (12.3)].

Data

Human data

Available human data are limited. Prospectively reported data (from clinical trials and postmarketing reports) from >150 pregnancies in patients treated with teriflunomide and >300 pregnancies in patients treated with leflunomide have not demonstrated an increased rate of congenital malformations or miscarriage following teriflunomide exposure in the early first trimester when followed by an accelerated elimination procedure. Specific patterns of major congenital malformations in humans have not been observed. Limitations of these data include an inadequate number of reported pregnancies from which to draw conclusions, the short duration of drug exposure in reported pregnancies, which precludes a full evaluation of the fetal risks, incomplete reporting, and the inability to control for confounders (such as underlying maternal disease and use of concomitant medications).

Animal data

When teriflunomide (oral doses of 1, 3, or 10 mg/kg/day) was administered to pregnant rats throughout the period of organogenesis, high incidences of fetal malformation (primarily craniofacial, and axial and appendicular skeletal defects) and fetal death were observed at doses not associated with maternal toxicity. Adverse effects on fetal development were observed following dosing at various stages throughout organogenesis. Maternal plasma exposure at the no-effect level (1.0 mg/kg/day) for fetal developmental toxicity in rats was less than that in humans at the maximum recommended human dose (MRHD, 14 mg/day).

Administration of teriflunomide (oral doses of 1, 3.5, or 12 mg/kg/day) to pregnant rabbits throughout organogenesis resulted in high incidences of fetal malformation (primarily craniofacial, and axial and appendicular skeletal defects) and fetal death at doses associated with minimal maternal toxicity. Maternal plasma exposure at the no-effect dose (1.0 mg/kg/day) for fetal developmental toxicity in rabbits was less than that in humans at the MRHD.

In studies in which teriflunomide (oral doses of 0.05, 0.1, 0.3, 0.6, or 1.0 mg/kg/day) was administered to rats during gestation and lactation, decreased growth, eye and skin abnormalities, and high incidences of malformation (limb defects) and postnatal death were observed in the offspring at doses not associated with maternal toxicity. Maternal plasma exposure at the no-effect dose for prenatal and postnatal developmental toxicity in rats (0.10 mg/kg/day) was less than that in humans at the MRHD.

In animal reproduction studies of leflunomide, embryolethality and teratogenic effects were observed in pregnant rat and rabbit at or below clinically relevant plasma teriflunomide exposures (AUC). In published reproduction studies in pregnant mice, leflunomide was embryolethal and increased the incidence of malformations (craniofacial, axial skeletal, heart and great vessel). Supplementation with exogenous uridine reduced the teratogenic effects in pregnant mice, suggesting that the mode of action (inhibition of mitochondrial enzyme dihydroorotate dehydrogenase) is the same for therapeutic efficacy and developmental toxicity.

At recommended doses in humans, teriflunomide and leflunomide result in a similar range of plasma concentrations of teriflunomide.

8.2 Lactation

Risk Summary

There are no data on the presence of teriflunomide in human milk, the effects on the breastfed infant, or the effects on milk production. Teriflunomide was detected in rat milk following a single oral dose. Because of the potential for adverse reactions in a breastfed infant from teriflunomide, women should not breastfeed during treatment with teriflunomide.

8.3 Females and Males of Reproductive Potential

Pregnancy Testing

Exclude pregnancy prior to initiation of treatment with teriflunomide in females of reproductive potential. Advise females to notify their healthcare provider immediately if pregnancy occurs or is suspected during treatment [see Warnings and Precautions (5.2, 5.3) and Use in Specific Populations (8.1)].

Contraception

Females

Females of reproductive potential should use effective contraception while taking teriflunomide. If teriflunomide is discontinued, use of contraception should be continued until it is verified that plasma concentrations of teriflunomide are less than 0.02 mg/L (0.02 mcg/mL, the level expected to have minimal fetal risk, based on animal data).

Females of reproductive potential who wish to become pregnant should discontinue teriflunomide and undergo an accelerated elimination procedure. Effective contraception should be used until it is verified that plasma concentrations of teriflunomide are less than 0.02 mg/L (0.02 mcg/mL) [see Warnings and Precautions (5.2, 5.3) and Use in Specific Populations (8.1)].

Males

Teriflunomide is detected in human semen. Animal studies to specifically evaluate the risk of male mediated fetal toxicity have not been conducted. To minimize any possible risk, men not wishing to father a child and their female partners should use effective contraception. Men wishing to father a child should discontinue use of teriflunomide and either undergo an accelerated elimination procedure or wait until verification that the plasma teriflunomide concentration is less than 0.02 mg/L (0.02 mcg/mL) [see Warnings and Precautions (5.3)].

8.4 Pediatric Use

Safety and effectiveness in pediatric patients have not been established. Effectiveness of teriflunomide for the treatment of relapsing form of multiple sclerosis in pediatric patients (10 to 17 years of age) was not established in an adequate and well-controlled clinical study in 166 patients (109 patients received once-daily doses of teriflunomide and 57 patients received placebo) for up to 96 weeks.

Pancreatitis has been reported in adults in the postmarketing setting, but appears to occur at higher frequency in the pediatric population. In this pediatric study, cases of pancreatitis were reported in 1.8% (2/109) of patients who received teriflunomide compared to no patients in the placebo group. All patients in the pediatric trial recovered or were recovering after treatment discontinuation and accelerated elimination procedure [see Warnings and Precautions (5.11)].

Additionally, elevated or abnormal blood creatine phosphokinase was reported in 6.4% of pediatric patients who received teriflunomide compared to no patients in the placebo group.

Juvenile Animal Toxicity Data

Oral administration of teriflunomide (0, 0.3, 3, or 6 mg/kg/day) to young rats on postnatal days 21 to 70 resulted in suppression of immune function (T-cell dependent antibody response) at the mid and high doses, and adverse effects on male reproductive organs (reduced sperm count) and altered neurobehavioral function (increased locomotor activity) at the high dose.

At the no-effect dose (0.3 mg/kg/day) for developmental toxicity in juvenile rats, plasma exposures were less than those in pediatric patients at the doses of teriflunomide tested in the clinical study.

8.5 Geriatric Use

Clinical studies of teriflunomide did not include patients over 65 years old.

8.6 Hepatic Impairment

No dosage adjustment is necessary for patients with mild and moderate hepatic impairment. The pharmacokinetics of teriflunomide in severe hepatic impairment has not been evaluated. Teriflunomide is contraindicated in patients with severe hepatic impairment [see Contraindications (4), Warnings and Precautions (5.1), and Clinical Pharmacology (12.3)].

8.7 Renal Impairment

No dosage adjustment is necessary for patients with mild, moderate, and severe renal impairment [see Clinical Pharmacology (12.3)].

10 OVERDOSAGE

There is no experience regarding teriflunomide overdose or intoxication in humans. Teriflunomide 70 mg daily up to 14 days was well tolerated by healthy subjects.

In the event of clinically significant overdose or toxicity, cholestyramine or activated charcoal is recommended to accelerate elimination [see Warnings and Precautions (5.3)].

11 DESCRIPTION

Teriflunomide is an oral de novo pyrimidine synthesis inhibitor of the DHO-DH enzyme, with the chemical name (Z)-2-Cyano-3-hydroxy-but-2-enoic acid-(4‑trifluoromethylphenyl)-amide. Its molecular weight is 270.21 and the molecular formula is C12H9F3N2O2 with the following chemical structure:

Teriflunomide is a white to almost white powder that is sparingly soluble in acetone, slightly soluble in methylene chloride, very slightly soluble in acetonitrile, insoluble in water, ethanol and isopropyl alcohol.

Teriflunomide is formulated as film-coated tablets for oral administration. Teriflunomide tablets contain 7 mg or 14 mg of teriflunomide and the following inactive ingredients: corn starch, colloidal silicon dioxide, hydroxypropyl cellulose, lactose monohydrate, magnesium stearate, microcrystalline cellulose and sodium starch glycolate. The film coating for the 14 mg tablet is made of hypromellose, polyethylene glycol, talc, titanium dioxide. In addition to these, the 7 mg tablet film coating contains iron oxide yellow.

12 CLINICAL PHARMACOLOGY

12.1 Mechanism of Action

Teriflunomide, an immunomodulatory agent with anti-inflammatory properties, inhibits dihydroorotate dehydrogenase, a mitochondrial enzyme involved in de novo pyrimidine synthesis. The exact mechanism by which teriflunomide exerts its therapeutic effect in multiple sclerosis is unknown but may involve a reduction in the number of activated lymphocytes in CNS.

12.2 Pharmacodynamics

Potential to Prolong the QT Interval

In a placebo-controlled thorough QT study performed in healthy adult subjects, there was no evidence that teriflunomide caused QT interval prolongation of clinical significance (i.e., the upper bound of the 90% confidence interval for the largest placebo-adjusted, baseline-corrected QTc was below 10 ms).

12.3 Pharmacokinetics

Teriflunomide is the principal active metabolite of leflunomide and is responsible for leflunomide's activity in vivo. At recommended doses, teriflunomide and leflunomide result in a similar range of plasma concentrations of teriflunomide.

Based on a population analysis of teriflunomide in healthy adult volunteers and adult MS patients, median t1/2 was approximately 18 and 19 days after repeated doses of 7 mg and 14 mg respectively. It takes approximately 3 months respectively to reach steady-state concentrations. The estimated AUC accumulation ratio is approximately 30 after repeated doses of 7 or 14 mg.

Absorption

Median time to reach maximum plasma concentrations is between 1 to 4 hours post dose following oral administration of teriflunomide.

Food does not have a clinically relevant effect on teriflunomide pharmacokinetics.

Distribution

Teriflunomide is extensively bound to plasma protein (>99%) and is mainly distributed in plasma. The volume of distribution is 11 L after a single intravenous (IV) administration.

Metabolism

Teriflunomide is the major circulating moiety detected in plasma. The primary biotransformation pathway to minor metabolites of teriflunomide is hydrolysis, with oxidation being a minor pathway. Secondary pathways involve oxidation, N-acetylation and sulfate conjugation.

Elimination

Teriflunomide is eliminated mainly through direct biliary excretion of unchanged drug as well as renal excretion of metabolites. Over 21 days, 60.1% of the administered dose is excreted via feces (37.5%) and urine (22.6%). After an accelerated elimination procedure with cholestyramine, an additional 23.1% was recovered (mostly in feces). After a single IV administration, the total body clearance of teriflunomide is 30.5 mL/h.

Drug Interaction Studies

Teriflunomide is not metabolized by Cytochrome P450 or flavin monoamine oxidase enzymes.

The potential effect of teriflunomide on other drugs

CYP2C8 substrates
There was an increase in mean repaglinide Cmax and AUC (1.7- and 2.4-fold, respectively) following repeated doses of teriflunomide and a single dose of 0.25 mg repaglinide, suggesting that teriflunomide is an inhibitor of CYP2C8 in vivo. The magnitude of interaction could be higher at the recommended repaglinide dose [see Drug Interactions (7)].

CYP1A2 substrates
Repeated doses of teriflunomide decreased mean Cmax and AUC of caffeine by 18% and 55%, respectively, suggesting that teriflunomide may be a weak inducer of CYP1A2 in vivo [see Drug Interactions (7)].

OAT3 substrates
There was an increase in mean cefaclor Cmax and AUC (1.43- and 1.54-fold, respectively), following repeated doses of teriflunomide, suggesting that teriflunomide is an inhibitor of organic anion transporter 3 (OAT3) in vivo[see Drug Interactions (7)].

BCRP and OATP1B1/1B3 substrates
There was an increase in mean rosuvastatin Cmax and AUC (2.65- and 2.51-fold, respectively) following repeated doses of teriflunomide, suggesting that teriflunomide is an inhibitor of BCRP transporter and organic anion transporting polypeptide 1B1 and 1B3 (OATP1B1/1B3) [see Drug Interactions (7)].

Oral contraceptives
There was an increase in mean ethinylestradiol Cmax and AUC0–24 (1.58- and 1.54-fold, respectively) and levonorgestrel Cmax and AUC0–24 (1.33- and 1.41-fold, respectively) following repeated doses of teriflunomide [see Drug Interactions (7)].

Teriflunomide did not affect the pharmacokinetics of bupropion (a CYP2B6 substrate), midazolam (a CYP3A4 substrate), S-warfarin (a CYP2C9 substrate), omeprazole (a CYP2C19 substrate), and metoprolol (a CYP2D6 substrate).

The potential effect of other drugs on teriflunomide

Potent CYP and transporter inducers: Rifampin did not affect the pharmacokinetics of teriflunomide.

Specific Populations

Hepatic impairment
Mild and moderate hepatic impairment had no impact on the pharmacokinetics of teriflunomide. The pharmacokinetics of teriflunomide in severe hepatic impairment has not been evaluated [see Contraindications (4), Warnings and Precautions (5.1), and Use in Specific Populations (8.6)].

Renal impairment
Severe renal impairment had no impact on the pharmacokinetics of teriflunomide [see Use in Specific Populations (8.7)].

Gender
In a population analysis, the clearance rate for teriflunomide is 23% less in females than in males.

Race
Effect of race on the pharmacokinetics of teriflunomide cannot be adequately assessed due to a low number of patients who self-identified as Black or African American, Asian, or other races in the clinical trials.

13 NONCLINICAL TOXICOLOGY

13.1 Carcinogenesis, Mutagenesis, Impairment of Fertility

Carcinogenesis

No evidence of carcinogenicity was observed in lifetime carcinogenicity bioassays in mouse and rat. In mouse, teriflunomide was administered orally at doses up to 12 mg/kg/day for up to 95 to 104 weeks; plasma teriflunomide exposures (AUC) at the highest dose tested are approximately 3 times that in humans at the maximum recommended human dose (MRHD, 14 mg/day). In rat, teriflunomide was administered orally at doses up to 4 mg/kg/day for up to 97 to 104 weeks; plasma teriflunomide AUCs at the highest doses tested are less than that in humans at the MRHD.

Mutagenesis

Teriflunomide was negative in the in vitro bacterial reverse mutation (Ames) assay, the in vitro HPRT assay, and in in vivo micronucleus and chromosomal aberration assays. Teriflunomide was positive in an in vitro chromosomal aberration assay in human lymphocytes, with and without metabolic activation. Addition of uridine (to supplement the pyrimidine pool) reduced the magnitude of the clastogenic effect; however, teriflunomide was positive in the in vitro chromosomal aberration assay, even in the presence of uridine.

4-Trifluoromethylaniline (4-TFMA), a minor metabolite of teriflunomide, was positive in the in vitro bacterial reverse mutation (Ames) assay, the in vitro HPRT assay, and the in vitro chromosomal aberration assay in mammalian cells. 4-TFMA was negative in in vivo micronucleus and chromosomal aberration assays.

Impairment of Fertility

Oral administration of teriflunomide (0, 1, 3, 10 mg/kg/day) to male rats prior to and during mating (to untreated females) resulted in no adverse effects on fertility; however, reduced epididymal sperm count was observed at the mid and high doses tested. The no-effect dose for reproductive toxicity in male rats (1 mg/kg) is less than the MRHD on a mg/m^2 basis.

Oral administration of teriflunomide (0, 0.84, 2.6, 8.6 mg/kg/day) to female rats, prior to and during mating (to untreated males) and continuing to gestation day 6, resulted in embryolethality, reduced fetal body weight, and/or malformations at all doses tested. Due to marked embryolethality at the highest dose tested, no fetuses were available for evaluation. The lowest dose tested is less than the MRHD on a mg/m^2 basis.

14 CLINICAL STUDIES

Four randomized, controlled, double-blind clinical trials established the efficacy of teriflunomide in patients with relapsing forms of multiple sclerosis.

Study 1 was a double-blind, placebo-controlled clinical trial that evaluated once daily doses of teriflunomide 7 mg and teriflunomide 14 mg for up to 26 months in patients with relapsing forms of multiple sclerosis. Patients were required to have a diagnosis of multiple sclerosis exhibiting a relapsing clinical course, with or without progression, and to have experienced at least one relapse over the year preceding the trial or at least two relapses over the two years preceding the trial. Patients were required not to have received interferon-beta for at least four months, or any other multiple sclerosis medication for at least six months before entering the study, nor were these medications permitted during the study. Neurological evaluations were to be performed at screening, every 12 weeks until week 108, and after suspected relapses. MRI was to be performed at screening, and at week 24, 48, 72, and 108. The primary endpoint was the annualized relapse rate (ARR).

In Study 1, 1088 patients were randomized to receive teriflunomide 7 mg (n=366), teriflunomide 14 mg (n=359), or placebo (n=363). At entry, patients had an Expanded Disability Status Scale (EDSS) score ≤5.5. Patients had a mean age of 38 years, mean disease duration of 5 years, and mean EDSS at baseline of 2.7. A total of 91% of patients had relapsing remitting multiple sclerosis, and 9% had a progressive form of multiple sclerosis with relapses. The mean duration of treatment was 635, 627, and 631 days for teriflunomide 7 mg, teriflunomide 14 mg, and placebo, respectively. The percentage of patients who completed the study treatment period was 75%, 73%, and 71% for teriflunomide 7 mg, teriflunomide 14 mg, and placebo, respectively.

There was a statistically significant reduction in ARR for patients who received teriflunomide 7 mg or teriflunomide 14 mg, compared to patients who received placebo (see Table 2). There was a consistent reduction of the ARR noted in subgroups defined by sex, age group, prior multiple sclerosis therapy, and baseline disease activity.

There was a statistically significant reduction in the relative risk of disability progression at week 108 sustained for 12 weeks (as measured by at least a 1-point increase from baseline EDSS ≤5.5 or a 0.5 point increase for those with a baseline EDSS >5.5) in the teriflunomide 14 mg group compared to placebo (see Table 2 and Figure 1).

The effect of teriflunomide on several magnetic resonance imaging (MRI) variables, including the total lesion volume of T2 and hypointense T1 lesions, was assessed in Study 1. The change in total lesion volume from baseline was significantly lower in the teriflunomide 7 mg and teriflunomide 14 mg groups than in the placebo group. Patients in both teriflunomide groups had significantly fewer gadolinium-enhancing lesions per T1-weighted scan than those in the placebo group (see Table 2).

Table 2: Clinical and MRI Results of Study 1
 | Teriflunomide 7 mg N=365 | Teriflunomide 14 mg N=358 | Placebo N=363
Clinical Endpoints
Annualized relapse rate | 0.370 (p = 0.0002) | 0.369 (p = 0.0005) | 0.539
Relative risk reduction | 31% | 31%
Percent of patients remaining relapse-free at week 108 | 53.7% | 56.5% | 45.6%
Percent disability progression at week 108 | 21.7% (p = 0.084) | 20.2% (p = 0.028) | 27.3%
Hazard ratio | 0.76 | 0.70
MRI Endpoints
Median change from baseline in Total lesion volume^1 (mL) at week 108 | 0.755 (p= 0.0317)^2 | 0.345 (p = 0.0003)^2 | 1.127
Mean number of Gd-enhancing T1-lesions per scan | 0.570 (p <0.0001) | 0.261 (p <0.0001) | 1.331

1. Total lesion volume: sum of T2 and hypointense T1 lesion volume in mL
2. p-values based on cubic root transformed data for total lesion volume

Figure 1: Kaplan-Meier Plot of Time to Disability Progression Sustained for 12 Weeks (Study 1)

Study 2 was a double-blind, placebo-controlled clinical trial that evaluated once daily doses of teriflunomide 7 mg and teriflunomide 14 mg for up to 40 months in patients with relapsing forms of multiple sclerosis. Patients were required to have a diagnosis of multiple sclerosis exhibiting a relapsing clinical course and to have experienced at least one relapse over the year preceding the trial, or at least two relapses over the two years preceding the trial. Patients were required not to have received any multiple sclerosis medication for at least three months before entering the trial, nor were these medications permitted during the trial. Neurological evaluations were to be performed at screening, every 12 weeks until completion, and after every suspected relapse. The primary end point was the ARR.

A total of 1165 patients received teriflunomide 7 mg (n=407), teriflunomide 14 mg (n=370), or placebo (n=388). Patients had a mean age of 38 years, a mean disease duration of 5 years, and a mean EDSS at baseline of 2.7. A total of 98% of patients had relapsing remitting multiple sclerosis, and 2% had a progressive form of multiple sclerosis with relapses. The mean duration of treatment was 552, 567, and 571 days for teriflunomide 7 mg, teriflunomide 14 mg, and placebo, respectively. The percentage of patients who completed the study treatment period was 67%, 66%, and 68% for teriflunomide 7 mg, teriflunomide 14 mg, and placebo, respectively.

There was a statistically significant reduction in the ARR for patients who received teriflunomide 7 mg or teriflunomide 14 mg compared to patients who received placebo (see Table 3). There was a consistent reduction of the ARR noted in subgroups defined by sex, age group, prior multiple sclerosis therapy, and baseline disease activity.

There was a statistically significant reduction in the relative risk of disability progression at week 108 sustained for 12 weeks (as measured by at least a 1-point increase from baseline EDSS ≤5.5 or a 0.5 point increase for those with a baseline EDSS >5.5) in the teriflunomide 14 mg group compared to placebo (see Table 3 and Figure 2).

Table 3: Clinical Results of Study 2
 | Teriflunomide 7 mg N=407 | Teriflunomide 14 mg N=370 | Placebo N=388
Clinical Endpoints
Annualized relapse rate | 0.389 (p = 0.0183) | 0.319 (p = 0.0001) | 0.501
Relative risk reduction | 22% | 36%
Percent of patients remaining relapse-free at week 108 | 58.2% | 57.1% | 46.8%
Percent disability progression at week 108 | 21.1% (p = 0.762) | 15.8% (p = 0.044) | 19.7%
Hazard ratio | 0.96 | 0.69

Figure 2: Kaplan-Meier Plot of Time to Disability Progression Sustained for 12 Weeks (Study 2)

Study 3 was a double-blind, placebo-controlled clinical trial that evaluated once daily doses of teriflunomide 7 mg and teriflunomide 14 mg for up to 108 weeks in patients with relapsing multiple sclerosis. Patients were required to have had a first clinical event consistent with acute demyelination occurring within 90 days of randomization with 2 or more T2 lesions at least 3 mm in diameter that were characteristic of multiple sclerosis. A total of 614 patients received teriflunomide 7 mg (n=203), teriflunomide 14 mg (n=214), or placebo (n=197). Patients had a mean age of 32 years, EDSS at baseline of 1.7, and mean disease duration of two months. The proportion of patients free of relapse was greater in the teriflunomide 7 mg (70.5%, p <0.05) and teriflunomide 14 mg (72.2%, p <0.05) groups than in the placebo group (61.7%).

The effect of teriflunomide on MRI activity was also demonstrated in Study 4, a randomized, double-blind, placebo-controlled clinical trial of multiple sclerosis patients with relapse. In Study 4, MRI was to be performed at baseline, 6 weeks, 12 weeks, 18 weeks, 24 weeks, 30 weeks, and 36 weeks after treatment initiation. A total of 179 patients were randomized to teriflunomide 7 mg (n=61), teriflunomide 14 mg (n=57), or placebo (n=61). Baseline demographics were consistent across treatment groups. The primary endpoint was the average number of unique active lesions/MRI scan during treatment. The mean number of unique active lesions per brain MRI scan during the 36-week treatment period was lower in patients treated with teriflunomide 7 mg (1.06) and teriflunomide 14 mg (0.98) as compared to placebo (2.69), the difference being statistically significant for both (p=0.0234 and p=0.0052, respectively).

16 HOW SUPPLIED/STORAGE AND HANDLING

Teriflunomide Tablets 7 mg are light yellow to yellow, biconvex, round film-coated tablets debossed with ‘G’ on one side and ‘43’ on the other side and are available as follows:

Carton of 28 (two blisters of 14 tablets), NDC 68462-423-15

Carton of 5 (one blister of 5 tablets), NDC 68462-423-85

Bottles of 30 with child-resistant closure, NDC 68462-423-30

Teriflunomide Tablets 14 mg are white to off-white, biconvex, round film-coated tablets debossed with ‘G’ on one side and ‘42’ on the other side and are available as follows:

Carton of 28 (two blisters of 14 tablets), NDC 68462-424-15

Carton of 5 (one blister of 5 tablets), NDC 68462-424-85

Bottles of 30 with child-resistant closure, NDC 68462-424-30

Store at 20°C to 25°C (68°F to 77°F); excursions permitted to 15°C to 30°C (59°F to 86°F) [see USP Controlled Room Temperature].

17 PATIENT COUNSELING INFORMATION

Advise the patient to read the FDA-approved patient labeling (Medication Guide).

A Medication Guide is required for distribution with teriflunomide tablets.

Hepatotoxicity

Inform patients that teriflunomide tablets may cause liver injury, which can be life-threatening, and that their liver enzymes will be checked before starting teriflunomide tablets and at least monthly for 6 months after starting teriflunomide tablets [see Dosage and Administration (2) and Warnings and Precautions (5.1)]. Advise patients that they should contact their physician if they have any unexplained nausea, vomiting, abdominal pain, fatigue, anorexia, or jaundice and/or dark urine.

Embryofetal Toxicity

- Advise females of reproductive potential
- of the potential for fetal harm if teriflunomide tablets are taken during pregnancy
- to notify their healthcare provider immediately if a pregnancy occurs or is suspected
- to use effective contraception during treatment with teriflunomide tablets and until the teriflunomide plasma concentration is verified to be less than 0.02 mg/L [see Warnings and Precautions (5.2, 5.3), Use in Specific Populations (8.1, 8.3), Clinical Pharmacology (12.3)].
- Instruct men taking teriflunomide tablets and not wishing to father a child to use effective contraception to minimize any possible risk to the fetus; their female partners should also use effective contraception.
- Advise men wishing to father a child to discontinue use of teriflunomide tablets and undergo an accelerated elimination procedure.

Availability of an Accelerated Elimination Procedure

Advise patients that teriflunomide may stay in the blood for up to 2 years after the last dose and that an accelerated elimination procedure may be used if needed [see Warnings and Precautions (5.3)].

Risk of Infections

Inform patients that they may develop a lowering of their white blood cell counts and that their blood counts will be checked before starting teriflunomide tablets.

Inform patients that they may be more likely to get infections when taking teriflunomide tablets and that they should contact their physician if they develop symptoms of infection, particularly in case of fever [see Warnings and Precautions (5.4)].

Advise patients that the use of some vaccines should be avoided during treatment with teriflunomide tablets and for at least 6 months after discontinuation.

Hypersensitivity Reactions

Advise patients to discontinue teriflunomide tablets and seek immediate medical attention if any signs or symptoms of a hypersensitivity reaction occur [see Contraindications (4) and Warnings and Precautions (5.5)]. Signs and symptoms can include dyspnea, urticaria, and angioedema involving the lips, eyes, throat, or tongue, or skin rash.

Serious Skin Reactions

Advise patients to discontinue teriflunomide tablets and seek immediate medical attention if any signs of a serious skin reaction, such as SJS or TEN, occur [see Warnings and Precautions (5.6)]. Signs and symptoms can include rash, mouth sores, blisters, or peeling skin.

DRESS/Multi-organ Hypersensitivity

Instruct patients and caregivers that a fever or rash associated with signs of other organ system involvement (e.g., lymphadenopathy, hepatic dysfunction) may be drug-related and should be reported to their healthcare provider immediately. Teriflunomide tablets should be discontinued immediately if a serious hypersensitivity reaction is suspected [see Warnings and Precautions (5.7)].

Peripheral Neuropathy

Inform patients that they may develop peripheral neuropathy. Advise patients that they should contact their physician if they develop symptoms of peripheral neuropathy, such as numbness or tingling of hands or feet [see Warnings and Precautions (5.8)].

Increased Blood Pressure

Inform patients that teriflunomide tablets may increase blood pressure [see Warnings and Precautions (5.9)].

Lactation

Advise females not to breastfeed during treatment with teriflunomide tablets [see Use in Specific Populations (8.2)].

Distributed by:

Glenmark Pharmaceuticals Inc., USA

Elmwood Park, NJ 07407

Questions? 1 (888) 721-7115

www.glenmarkpharma-us.com

August 2025

Medication Guide

Teriflunomide
(ter i FLOO noe mide)
tablets, for oral use

Read this Medication Guide before you start using teriflunomide tablets and each time you get a refill. There may be new information. This information does not take the place of talking with your doctor about your medical condition or your treatment.

What is the most important information I should know about teriflunomide tablets?

Teriflunomide tablets may cause serious side effects, including:

- Liver problems: Teriflunomide tablets may cause serious liver problems, including liver failure that can be life-threatening and may require a liver transplant. Your risk of developing serious liver problems may be higher if you already have liver problems or take other medicines that also affect your liver. Your doctor should do blood tests to check your liver:
- within 6 months before you start taking teriflunomide tablets
- 1 time a month for 6 months after you start taking teriflunomide tablets
Call your doctor right away if you have any of the following symptoms of liver problems:

Teriflunomide may stay in your blood for up to 2 years after you stop taking it. Your doctor can prescribe a medicine to help lower your blood levels of teriflunomide more quickly. Talk to your doctor if you want more information about this.

What are teriflunomide tablets?

- Teriflunomide tablets are a prescription medicine used to treat relapsing forms of multiple sclerosis (MS), to include clinically isolated syndrome, relapsing-remitting disease, and active secondary progressive disease, in adults.
- It is not known if teriflunomide tablets are safe and effective in children.

Who should not take teriflunomide tablets?

Do not take teriflunomide tablets if you:

- have severe liver problems.
- are pregnant or are of childbearing age and not using effective birth control.
- have had an allergic reaction to leflunomide, teriflunomide, or any other ingredients in teriflunomide tablets. Please see the end of this Medication Guide for a complete list of ingredients in teriflunomide tablets.
- take a medicine called leflunomide.

What should I tell my doctor before taking teriflunomide tablets?

Before you take teriflunomide tablets, tell your doctor about all of your medical conditions, including if you:

- have liver or kidney problems.
- have a fever or infection, or you are unable to fight infections.
- have numbness or tingling in your hands or feet that is different from your MS symptoms.
- have diabetes.
- have had serious skin problems when taking other medicines.
- have breathing problems.
- have high blood pressure.
- are breastfeeding or plan to breastfeed. It is not known if teriflunomide passes into your breast milk. You and your doctor should decide if you will take teriflunomide tablets or breastfeed. You should not do both.

Tell your doctor about all the medicines you take, including prescription and over-the-counter medicines, vitamins, and herbal supplements. Using teriflunomide tablets and other medicines may affect each other causing serious side effects. Teriflunomide tablets may affect the way other medicines work, and other medicines may affect how teriflunomide tablets work.

Especially tell your doctor if you take medicines that could raise your chance of getting infections, including medicines used to treat cancer or to control your immune system.

Ask your doctor or pharmacist for a list of these medicines if you are not sure.

Know the medicines you take. Keep a list of them to show your doctor or pharmacist when you get a new medicine.

How should I take teriflunomide tablets?

- Take teriflunomide tablets exactly as your doctor tells you to take it.
- Take teriflunomide tablets 1 time each day.
- Take teriflunomide tablets with or without food.

What are possible side effects of teriflunomide tablets?

Teriflunomide tablets may cause serious side effects, including:

- see "What is the most important information I should know about teriflunomide tablets?"
- decreases in your white blood cell count. Your white blood cell counts should be checked before you start taking teriflunomide tablets. When you have a low white blood cell count you:
  - may have more frequent infections. You should have a skin test for TB (tuberculosis) before you start taking teriflunomide tablets. Tell your doctor if you have any of these symptoms of an infection:
    - fever
    - tiredness
    - body aches
    - chills
    - nausea
    - vomiting
  - should not receive certain vaccinations during your treatment with teriflunomide tablets and for 6 months after your treatment with teriflunomide tablets ends.
- allergic reactions. Stop taking teriflunomide tablets and call your doctor right away or get emergency medical help if you have difficulty breathing, itching, swelling on any part of your body including in your lips, eyes, throat, or tongue.
- serious skin reactions. Teriflunomide tablets may cause serious skin reactions that may lead to death. Stop taking teriflunomide tablets and call your doctor right away or get emergency medical help if you have any of the following symptoms: rash or redness and peeling, mouth sores or blisters.
- other types of allergic reactions or serious problems that may affect different parts of the body such as your liver, kidneys, heart, or blood cells. You may or may not have a rash with these types of reactions. Other symptoms you may have are:
  - severe muscle pain
  - swollen lymph glands
  - swelling of your face
  - unusual bruising or bleeding
  - weakness or tiredness
  - yellowing of your skin or the white part of your eyes

If you have a fever or rash with any of the above symptoms, stop taking teriflunomide tablets and call your doctor right away.

- numbness or tingling in your hands or feet that is different from your MS symptoms. You have a higher chance of getting these symptoms if you:
- are over 60 years of age
- take certain medicines that affect your nervous system
- have diabetes
Tell your doctor if you have numbness or tingling in your hands or feet that is different from your MS.

The most common side effects of teriflunomide tablets include:

- headache
- diarrhea
- nausea
- hair thinning or loss (alopecia)
- increases in the results of blood tests to check your liver function

These are not all the possible side effects of teriflunomide tablets. For more information, ask your doctor or pharmacist.

Call your doctor for medical advice about side effects. You may report side effects to FDA at 1-800-FDA-1088.

How should I store teriflunomide tablets?

- Store teriflunomide tablets at room temperature between 68°F to 77°F (20°C to 25°C).
- Keep teriflunomide tablets and all medicines out of the reach of children.

General information about the safe and effective use of teriflunomide tablets.

Medicines are sometimes prescribed for purposes other than those listed in a Medication Guide. Do not use teriflunomide tablets for a condition for which it was not prescribed. Do not give teriflunomide tablets to other people, even if they have the same symptoms you have. It may harm them.

You can ask your doctor or pharmacist for information about teriflunomide tablets that is written for health professionals.

What are the ingredients in teriflunomide tablets?

Active ingredient: teriflunomide

Inactive ingredients in 7 mg and 14 mg tablets: corn starch, colloidal silicon dioxide, hydroxypropyl cellulose, hypromellose, lactose monohydrate, magnesium stearate, microcrystalline cellulose, polyethylene glycol, sodium starch glycolate, talc, titanium dioxide. In addition, the 7 mg tablets also contain iron oxide yellow.

For more information, call Glenmark Pharmaceuticals Inc., USA at 1 (888) 721-7115.

Distributed by:

Glenmark Pharmaceuticals Inc., USA

Elmwood Park, NJ 07407

Questions? 1 (888) 721-7115

www.glenmarkpharma-us.com

This Medication Guide has been approved by the U.S. Food and Drug Administration. Revised: August 2025

Package/Label Display Panel

NDC 68462-423-30

Teriflunomide Tablets

7 mg

Pharmacist: Dispense the Medication Guide provided separately to each patient.

Rx only

30 Tablets

Package/Label Display Panel

NDC 68462-424-30

Teriflunomide Tablets

14 mg

Pharmacist: Dispense the Medication Guide provided separately to each patient.

Rx only

30 Tablets